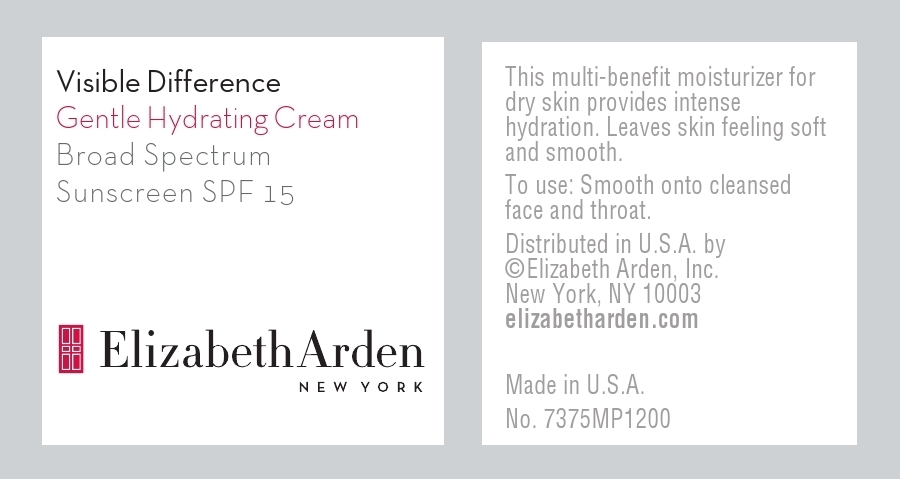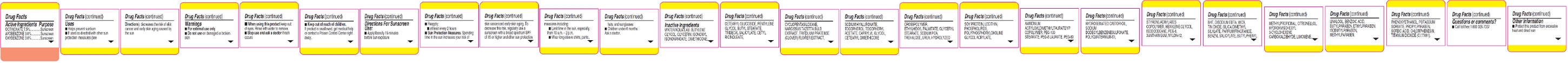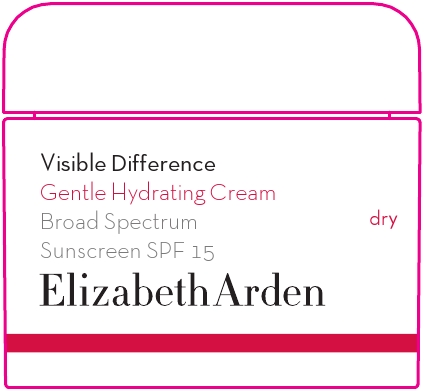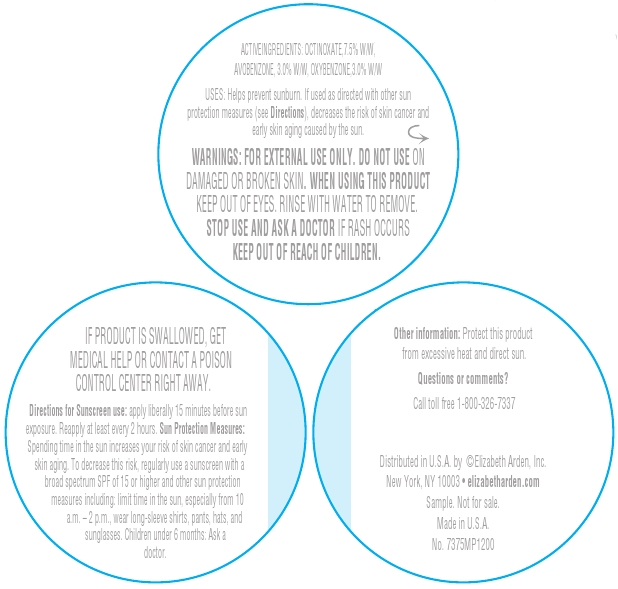 DRUG LABEL: Visible Difference Gentle Hydrating Broad Spectrum Sunscreen SPF 15
NDC: 67938-1169 | Form: CREAM
Manufacturer: Elizabeth Arden, Inc
Category: otc | Type: HUMAN OTC DRUG LABEL
Date: 20130501

ACTIVE INGREDIENTS: OCTINOXATE 3.75 g/50 g; AVOBENZONE 1.5 g/50 g; OXYBENZONE 1.5 g/50 g
INACTIVE INGREDIENTS: WATER; BUTYLENE GLYCOL; GLYCERIN; ISONONYL ISONONANOATE; DIMETHICONE; CETEARYL GLUCOSIDE; PENTYLENE GLYCOL; BUTYL STEARATE; TRIDECYL SALICYLATE; CETYL RICINOLEATE; CYCLOMETHICONE 5; NARCISSUS TAZETTA BULB; TRIFOLIUM PRATENSE FLOWER; HYALURONATE SODIUM; TOCOPHEROL; .ALPHA.-TOCOPHEROL ACETATE; CAPRYLYL GLYCOL; ETHYLHEXYL PALMITATE; GLYCERYL MONOSTEARATE; SODIUM PYRROLIDONE CARBOXYLATE; TREHALOSE; UREA; AMMONIUM ACRYLOYLDIMETHYLTAURATE/VP COPOLYMER; PEG-100 STEARATE; PEG-8 LAURATE; SODIUM DODECYLBENZENESULFONATE; HEXYLENE GLYCOL; ISODODECANE; POLYETHYLENE GLYCOL 400; XANTHAN GUM; NYLON-12; BUTYLATED HYDROXYTOLUENE; EDETATE DISODIUM; MICA; STANNIC OXIDE; SILICA DIMETHYL SILYLATE; BENZYL SALICYLATE; BUTYLPHENYL METHYLPROPIONAL; HYDROXYISOHEXYL 3-CYCLOHEXENE CARBOXALDEHYDE; BENZOIC ACID; BUTYLPARABEN; ISOBUTYLPARABEN; METHYLPARABEN; PHENOXYETHANOL; POTASSIUM SORBATE; PROPYLPARABEN; SORBIC ACID; CHLORPHENESIN; TITANIUM DIOXIDE

BC1169

DESCRIPTION

This multi-benefit moisturizer for dry skin provides intense hydration. Leaves skin feeling soft and smooth.

INDICATIONS AND USAGE

To Use: Smooth onto cleansed face and throat.

Directions For Sunscreen Use: Apply liberally 15 minutes before sun exposure. Reapply at least every 2 hours. Sun Protection Measures. Spending time in the sun increases your risk of measures including: Limit time in the sun, especially from 10 a.m. – 2 p.m. Wear long-sleeve shirts, pants, decrease this risk, regularly use a sunscreen with a broad spectrum SPF of 15 or higher and other sun protection hats, and sunglasses.

Children under 6 months ask a doctor.

WARNINGS

Warnings: For external use only. Do not use on damaged or broken skin. When using this product keep out of eyes. Rinse with water to remove. Stop use and ask a doctor if rash occurs.

OTC - ACTIVE INGREDIENT

Active Ingredients: Octinoxate 7.5%, Avobenzone 3.0%, Oxybenzone 3.0%.

INACTIVE INGREDIENT

Inactive Ingredients: Water/Aqua/Eau, Butylene Glycol, Glycerin, Isononyl Isononanoate, Dimethicone, Cetearyl Glucoside, Pentylene Glycol, Butyl Stearate, Tridecyl Salicylate, Cetyl Ricinoleate, Cyclopentasiloxane, Narcissus Tazetta Bulb Extrat, Trifolium Pratense (Clover) Flower Extract, Sodium Hyaluronate, Tocopherol, Tocopheryl Acetate, Caprylyl Glycol, Cetearyl Dimethicone Crosspolymer, Ethylhexyl Palmitate, Glyceryl Stearate, Sodium PCA, Trehalose, Urea, Hyrdolyzed Soy Protein, Lecithin, Phospholipids, Polyphophorylcholine Glycol Acrylate, Ammonium Acryloyldimethylaurate/VP Coplymer, PEG-100 Stearate, PEG-8 Laurate, PEG-60 Hydrogenated Castor Oil, Sodium Dodecylbenzenesulfonate, Polyquaternium-51, Styrene/Acrylates Copolymer, Hexylene Glycol, Isododecane, PEG-8, Xanthan Gum, Nylon-12, BHT, Disodium EDTA, Mica, Tin Oxide, Silica Dimethyl Silylate, Parfum/Fragrance, Benzyl Salicylate, Butylphenyl Methylpropional, Citonellol, Hydroxyisohexyl 3-Cyclohexene Carboxaldehyde, Limnene, Linalool, Benzoic Acid, Butylparaben, Ethylparaben, Isobutylparaben, Methylparaben, Phenoxyethanol, Potassium Sorbate, Propylparaben, Sorbic Acid, Chlorphenesin, Titanium Dioxide (CI 77891).

DOSAGE AND ADMINISTRATION

Smooth on to face and throat.

OTC - KEEP OUT OF REACH OF CHILDREN

Keep out of reach of children. If product is swallowed, get medical help or contact a Poison Control Center right away.

OTC - PURPOSE

Provides SPF 15 Sun Protection.

WHEN USING

Keep out of eyes.